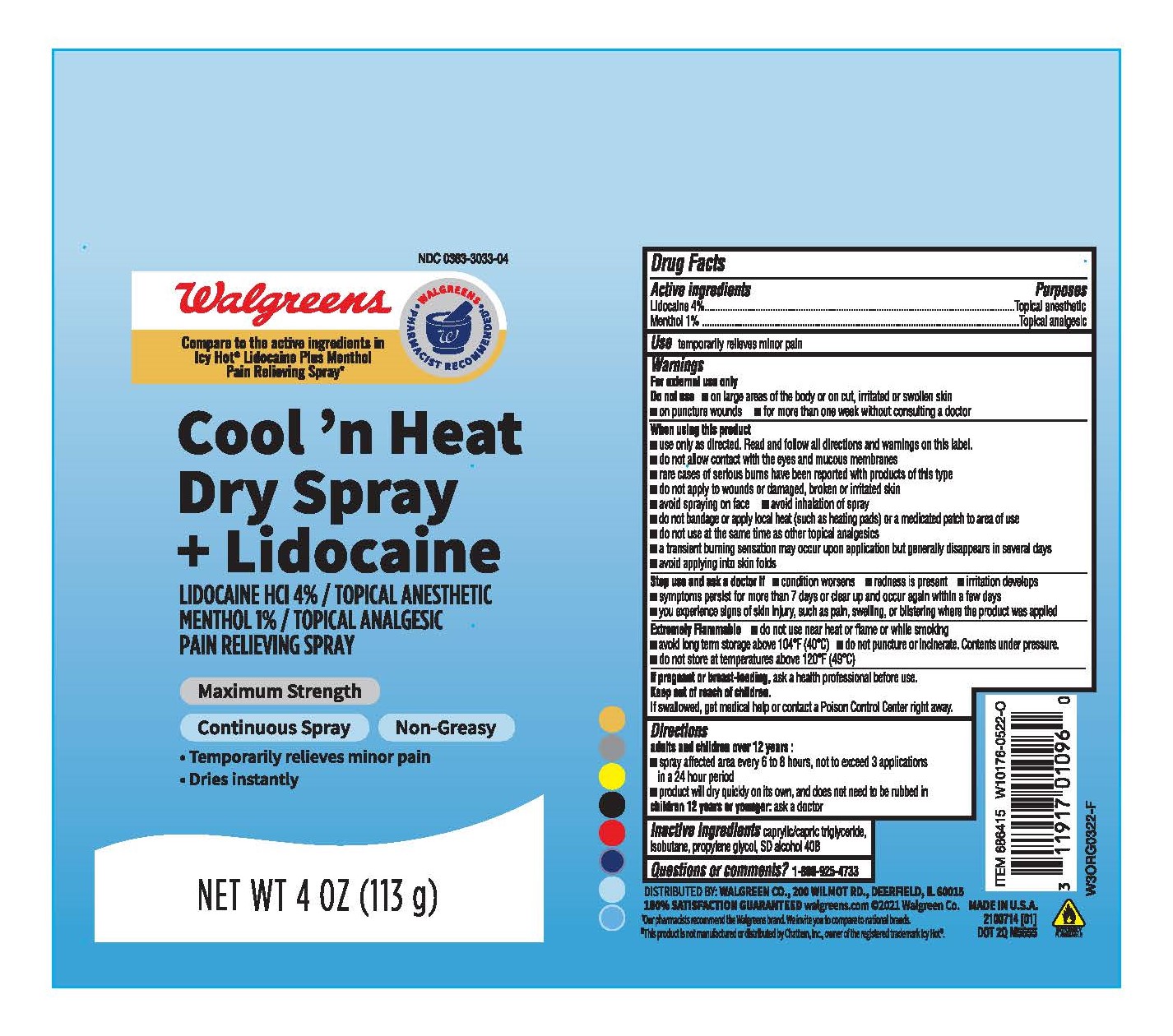 DRUG LABEL: Walgreens Cool n heat
NDC: 0363-3033 | Form: AEROSOL, SPRAY
Manufacturer: Walgreens
Category: otc | Type: HUMAN OTC DRUG LABEL
Date: 20231031

ACTIVE INGREDIENTS: LIDOCAINE 4 g/100 g; MENTHOL 1 g/100 g
INACTIVE INGREDIENTS: PROPYLENE GLYCOL; MEDIUM-CHAIN TRIGLYCERIDES; ISOBUTANE; DEHYDRATED ALCOHOL

Walgreens cool n heat Dry Spray

ACTIVE INGREDIENT

Lidocaine 4%

Menthol 1%

PURPOSE

Topical Anesthetic

Topical Analgesic

INDICATIONS AND USAGE

Temporarily relieves minor pain

WARNINGS

For External Use Only

Do not use:

- on large areas of the body or on cut, irritated or swollen skin
- on puncture wounds
- for more than one week without consulting a doctor

Extremely Flammable:

- Do not use near heat or flame or while smoking
- Avoid long term storage above 104° F (40°C)
- do not puncture or incinerate. Contents under pressure.
- do not store at temperatures above 120° F (49°C)

When using this product:

- use only as directed. Read and follow all directions and warnings on this label
- do not allow contact with the eyes and mucous membranes
- rare cases of serious burns have been reported with products of this type
- do not apply to wounds or damaged, broken or irritated skin
- avoid spraying on face
- avoid inhalation of spray
- do not bandage or apply local heat (such as heating pads) or a medicated patch to area of use
- do not use the same time as other topical analgesics
- a transient burning sensation may occur upon application but generally disappears in several days
- avoid applying into skin folds

Stop use and ask a doctor if:

- conditions worsens
- redness is present
- irritation develops
- symptoms persist for more than 7 days or clear up and occur again within a few days
- you experience signs of skin injury, such as pain, swelling, or blistering where the product was applied

PREGNANCY OR BREAST FEEDING

If Pregnant or breast feeding, ask a health professional before use.

Keep out of reach of children.

If swallowed, get medical help or contact a poison Control Center right away

DOSAGE AND ADMINISTRATION

Adults and Children over 12 years:

- Spray affected area every 6 to 8 hours, not to exceed 3 applications in a 24-hour period
- Product will dry quickly on its own, and does not need to be rubbed in

Children 12 years and younger: Ask a doctor

INACTIVE INGREDIENT

caprylic/capric triglyceride, isobutane, propylene glycol, SD alcohol 40B (30%)

QUESTIONS

1-800-925-4733